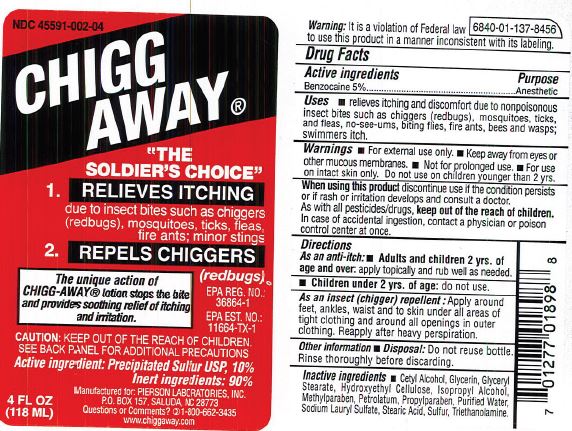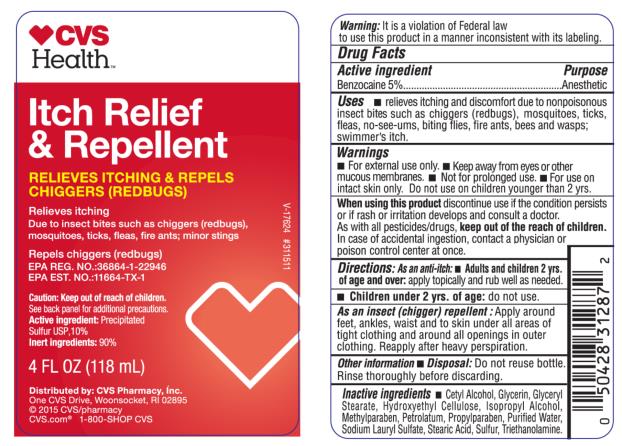 DRUG LABEL: Chigg Away
NDC: 82645-918 | Form: LOTION
Manufacturer: Pharma Nobis, LLC
Category: otc | Type: HUMAN OTC DRUG LABEL
Date: 20250724

ACTIVE INGREDIENTS: BENZOCAINE 50 mg/1 mL
INACTIVE INGREDIENTS: CETYL ALCOHOL; GLYCERIN; GLYCERYL MONOSTEARATE; HYDROXYETHYL CELLULOSE (1500 MPA.S AT 1%); ISOPROPYL ALCOHOL; METHYLPARABEN; PETROLATUM; PROPYLPARABEN; WATER; SODIUM LAURYL SULFATE; STEARIC ACID; SULFUR; TROLAMINE

Private Label Chigg Away

CVS Itch Relief & Repellent

Drug Facts

Active Ingredient

Benzocaine 5%

Purpose

Anesthetic

Use

Relieves itching and discomfort due to nonpoisonous insect bites such as chiggers (redbugs), mosquitoes, ticks, fleas, no-see-ums, biting flies, fire ants, bees and wasps; summer’s itch.

Warnings

For external use only. Keep away from eyes or other mucous membranes. Not for prolonged use. For use on intact skin only. Do not use on children younger than 2 yrs.

When using this product

discontinue use if the condition persists or if a rash or irritation develops and consult a doctor. As with all pesticides/drugs,

keep out of the reach of children.

In case of accidental ingestion, contact physician or poison control center at once.

Directions: As an anti-itch.

- Adults and children 2 yrs. of age and over. Apply topically and rub well as needed.
- Children under 2 yrs. of age: Do not use

As an insect (chigger) repellent: Apply around feet, ankles, waist and to skin under all areas of tight clothing and around all openings in outer clothing. Reapply after heavy perspiration.

Other Information

- Disposal: Do not reuse bottle. Rinse thoroughly before discarding.

Inactive Ingredient

Cetyl alcohol. Glycerin, Glyceryl stearate, Hydroxyethyl cellulose, Isopropyl alcohol, Methylparaben, Petrolatum, Propylparaben, Purified water, Sodium lauryl sulfate, Stearic acid, Sulfur, and Triothanolamine..